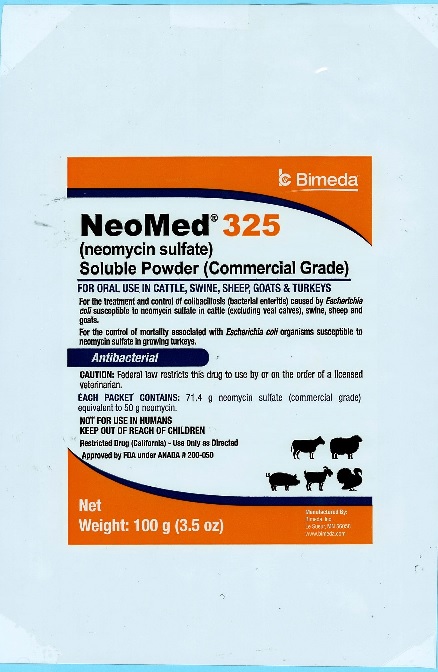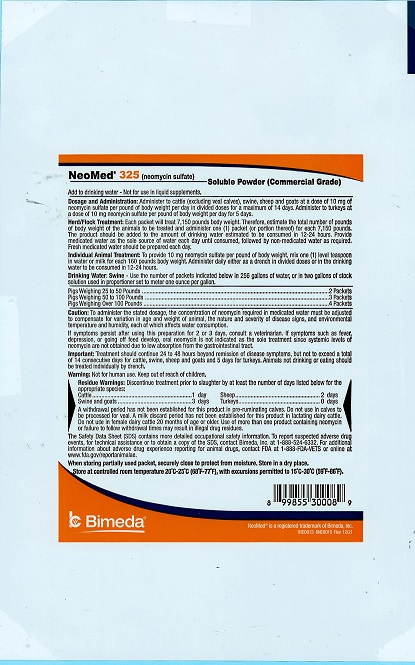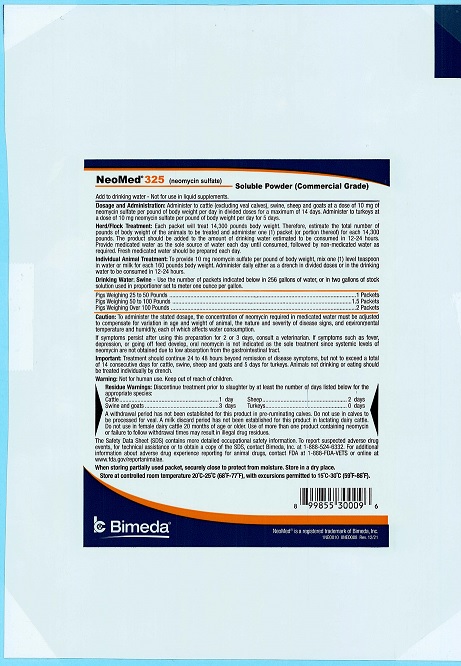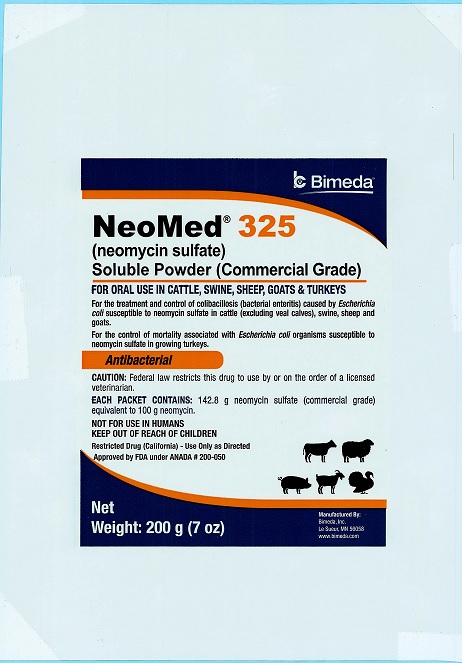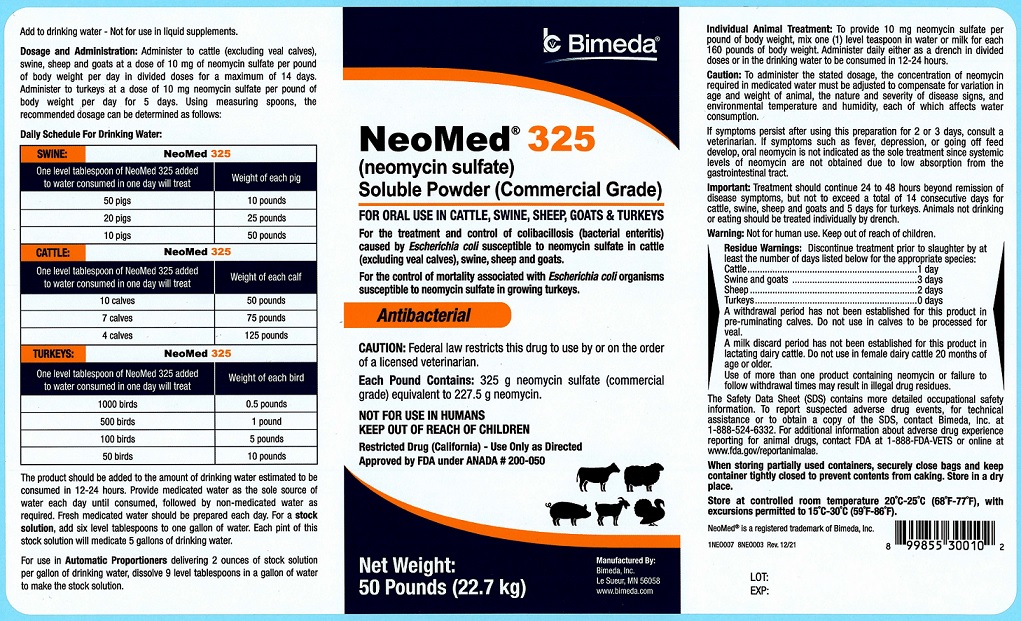 DRUG LABEL: NeoMed 325
NDC: 61133-5442 | Form: POWDER, FOR SOLUTION
Manufacturer: Bimeda, Inc.
Category: animal | Type: PRESCRIPTION ANIMAL DRUG LABEL
Date: 20240328

ACTIVE INGREDIENTS: NEOMYCIN SULFATE 227.5 g/0.454 kg

100 g pouch

NeoMed® 325
(neomycin sulfate)
Soluble Powder (Commercial Grade)
FOR ORAL USE IN CATTLE, SWINE, SHEEP, GOATS & TURKEYS

For the treatment and control of colibacillosis (bacterial enteritis) caused by Escherichia coli susceptible to neomycin sulfate in cattle (excluding veal calves), swine, sheep and goats.
For the control of mortality associated with Escherichia coli organisms susceptible to neomycin sulfate in growing turkeys.
Antibacterial

CAUTION: Federal law restricts this drug to use by or on the order of a licensed veterinarian.

Each Packet Contains: 71.4 g neomycin sulfate (commercial grade) equivalent to 50 g neomycin.

NOT FOR USE IN HUMANS
KEEP OUT OF REACH OF CHILDREN
Restricted Drug (California)- Use Only as Directed

Approved by FDA under ANADA # 200-050

NET WEIGHT:
100 g (3.5 oz)

100 g pouch

Add to drinking water - Not for use in liquid supplements.

DOSAGE AND ADMINISTRATION: Administer to cattle (excluding veal calves), swine, sheep and goats at a dose of 10 mg of neomycin sulfate per pound of body weight per day in divided doses for a maximum of 14 days. Administer to turkeys at a dose of 10 mg neomycin sulfate per pound of body weight per day for 5 days.

Herd/Flock Treatment: Each packet will treat 7,150 pounds body weight. Therefore, estimate the total number of pounds of body weight of the animals to be treated and administer one (1) packet (or portion thereof) for each 7,150 pounds. The product should be added to the amount of drinking water estimated to be consumed in 12-24 hours. Provide medicated water as the sole source of water each day until consumed, followed by non-medicated water as required. Fresh medicated water should be prepared each day.

Individual Animal Treatment: To provide 10 mg neomycin sulfate per pound of body weight, mix one (1) level teaspoon in water or milk for each 160 pounds of body weight. Administer daily either as a drench in divided doses or in the drinking water to be consumed in 12-24 hours.

Drinking Water: Swine Use the number of packets indicated below in 256 gallons of water, or in two gallons of stock solution used in proportioner set to meter one ounce per gallon.

Pigs Weighing 25 to 50 Pounds | 2 Packets
Pigs Weighing 50 to 100 Pounds | 3 Packets
Pigs Weighing Over 100 Pounds | 4 Packets

200 g Pouch

NeoMed® 325
(neomycin sulfate)
Soluble Powder (Commercial Grade)
FOR ORAL USE IN CATTLE, SWINE, SHEEP, GOATS & TURKEYS

For the treatment and control of colibacillosis (bacterial enteritis) caused by Escherichia coli susceptible to neomycin sulfate in cattle (excluding veal calves), swine, sheep and goats.
For the control of mortality associated with Escherichia coli organisms susceptible to neomycin sulfate in growing turkeys.
Antibacterial

CAUTION: Federal law restricts this drug to use by or on the order of a licensed veterinarian.

Each Packet Contains: 142.8 g neomycin sulfate (commercial grade) equivalent to 100 g neomycin.

NOT FOR USE IN HUMANS
KEEP OUT OF REACH OF CHILDREN
Restricted Drug (California)- Use Only as Directed

Approved by FDA under ANADA # 200-050

NET WEIGHT:
200 g (7 oz)

200 g Pouch

Add to drinking water - Not for use in liquid supplements.
DOSAGE AND ADMINISTRATION: Administer to cattle (excluding veal calves), swine, sheep and goats at a dose of 10 mg of neomycin sulfate per pound of body weight per day in divided doses for a maximum of 14 days. Administer to turkeys at a dose of 10 mg neomycin sulfate per pound of body weight per day for 5 days.
Herd/Flock Treatment: Each packet will treat 14,300 pounds body weight. Therefore, estimate the total number of pounds of body weight of the animals to be treated and administer one (1) packet (or portion thereof) for each 14,300 pounds. The product should be added to the amount of drinking water estimated to be consumed in 12-24 hours. Provide medicated water as the sole source of water each day until consumed, followed by non-medicated water as required. Fresh medicated water should be prepared each day.
Individual Animal Treatment: To provide 10 mg neomycin sulfate per pound of body weight, mix one (1) level teaspoon in water or milk for each 160 pounds of body weight. Administer daily either as a drench in divided doses or in the drinking water to be consumed in 12-24 hours.
Drinking Water: Swine Use the number of packets indicated below in 256 gallons of water, or in two gallons of stock solution used in proportioner set to meter one ounce per gallon.

Pigs Weighing 25-50 Pounds | 1 Packet
Pigs Weighing 50 to 100 Pounds | 1.5 Packets
Pigs Weighing Over 100 Pounds | 2 Packets

50 Pounds

NeoMed® 325
(neomycin sulfate)
Soluble Powder (Commercial Grade)
FOR ORAL USE IN CATTLE, SWINE, SHEEP, GOATS & TURKEYS

For the treatment and control of colibacillosis (bacterial enteritis) caused by Escherichia coli susceptible to neomycin sulfate in cattle (excluding veal calves), swine, sheep and goats.
For the control of mortality associated with Escherichia coli organisms susceptible to neomycin sulfate in growing turkeys.
Antibacterial

CAUTION: Federal law restricts this drug to use by or on the order of a licensed veterinarian.

Each Pound Contains: 325 g neomycin sulfate (commercial grade) equivalent to 227.5 g neomycin.

NOT FOR USE IN HUMANS
KEEP OUT OF REACH OF CHILDREN
Restricted Drug (California)- Use Only as Directed

Approved by FDA under ANADA # 200-050

NET WEIGHT:
50 Pounds (22.7 kg)

50 Pounds

Add to drinking water - Not for use in liquid supplements.
Dosage and Administration: Administer to cattle (excluding veal calves), swine, sheep and goats at a dose of 10 mg of neomycin sulfate per pound of body weight per day in divided doses for a maximum of 14 days. Administer to turkeys at a dose of 10 mg neomycin sulfate per pound of body weight per day for 5 days. Using measuring spoons, the recommended dosage can be determined as follows:

Daily Schedule For Drinking Water:

SWINE
One level tablespoon of NeoMed 325 added to water consumed in one day will treat | Weight of each pig
50 pigs | 10 pounds
20 pigs | 25 pounds
10 pigs | 50 pounds

CATTLE
One level tablespoon of NeoMed 325 added to water consumed in one day will treat | Weight of each calf
10 calves | 50 pounds
7 calves | 75 pounds
4 calves | 125 pounds

TURKEYS
One level tablespoon of NeoMed 325 added to water consumed in one day will treat | Weight of each bird
1000 birds | 0.5 pounds
500 birds | 1 pounds
100 birds | 5 pounds
50 birds | 10 pounds

The product should be added to the amount of drinking water estimated to be consumed in 12-24 hours. Provide medicated water as the sole source of water each day until consumed, followed by non-medicated water as required. Fresh medicated water should be prepared each day. For a stock solution, add six level tablespoons to one gallon of water. Each pint of this stock solution will medicate 5 gallons of drinking water.
For use in Automatic Proportioners delivering 2 ounces of stock solution per gallon of drinking water, dissolve 9 level tablespoons in a gallon of water to make the stock solution.

Individual Animal Treatment: To provide 10 mg neomycin sulfate per pound of body weight, mix one (1) level teaspoon in water or milk for each 160 pounds of body weight. Administer daily either as a drench in divided doses or in the drinking water to be consumed in 12-24 hours.

WARNINGS AND PRECAUTIONS

Caution: To administer the stated dosage, the concentration of neomycin required in medicated water must be adjusted to compensate for variation in age and weight of animal, the nature and severity of disease signs, and environmental temperature and humidity, each of which affects water consumption.

If symptoms persist after using this preparation for 2 or 3 days, consult a veterinarian. If symptoms such as fever, depression, or going off feed develop, oral neomycin is not indicated as the sole treatment since systemic levels of neomycin are not obtained due to low absorption from the gastrointestinal tract.

Important: Treatment should continue 24 to 48 hours beyond remission of disease symptoms, but not to exceed a total of 14 consecutive days for cattle, swine, sheep and goats and 5 days for turkeys. Animals not drinking or eating should be treated individually by drench.

Warning: Not for human use. Keep out of reach of children.

RESIDUE WARNING

Residue Warnings: Discontinue treatment prior to slaughter by at least the number of days listed below for appropriate species:

Cattle | 1 day
Swine and Goats | 3 days
Sheep | 2 days
Turkeys | 0 days

A withdrawal period has not been established for this product in pre-ruminating calves. Do not use in calves to be processed for veal. A milk discard period has not been established for this product in lactating dairy cattle. Do not use in female dairy cattle 20 months of age or older. Use of more than one product containing neomycin or failure to follow withdrawal times may result in illegal drug residues.

The Safety Data Sheet (SDS) contains more detailed occupational safety information. To report suspected adverse drug events, for technical assistance or to obtain a copy of the SDS, contact Bimeda, Inc. at 1-888-524-6332. For additional information about adverse drug experience reporting for animal drugs, contact FDA at 1-888-FDA-VETS or online at www.fda.gov/reportanimalae.

100 g and 200 g Pouches

When storing partially used packet, securely close protect from moisture. Store in a dry place.

Store at controlled room temperature 20°C-25°C (68°F-77°F), with excursions permitted to
15°C- 30°C (59°-86°F).

50 Pounds

When storing partially used containers, securely close bags and keep container tightly closed to prevent contents from caking. Store in a dry place.

Store at controlled room temperature 20°C-25°C (68°F-77°F), with excursions permitted to
15°C- 30°C (59°-86°F).